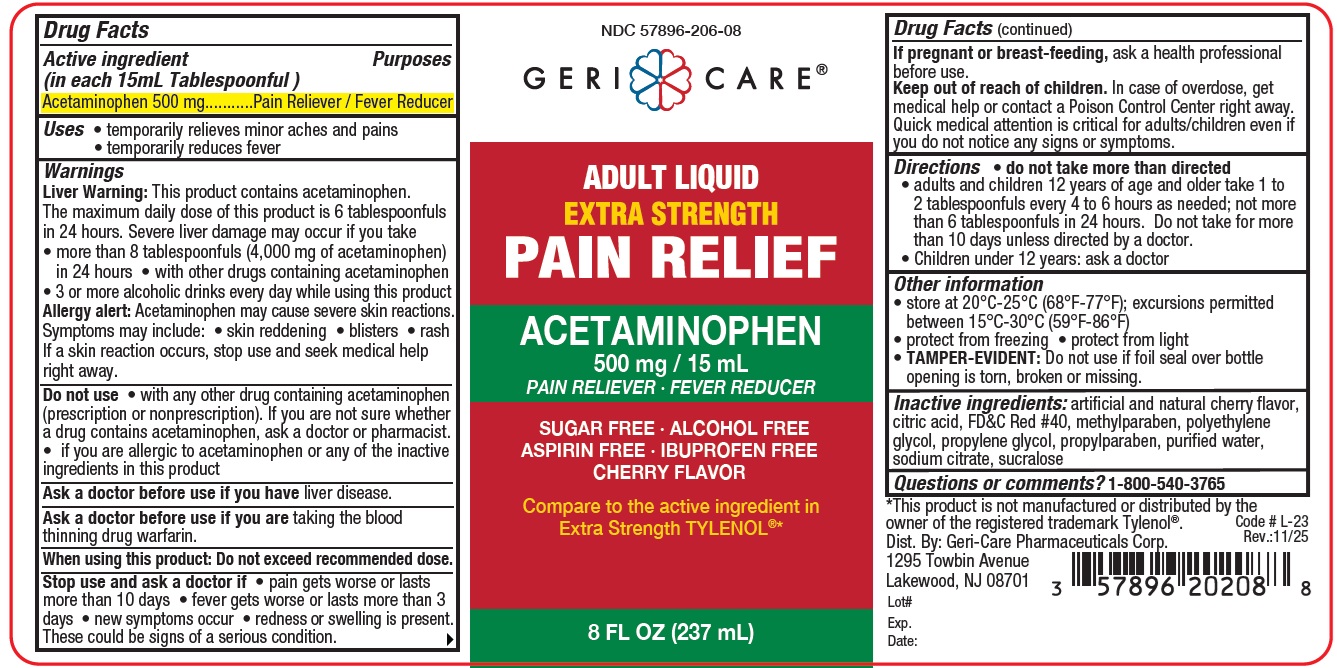 DRUG LABEL: EXTRA STRENGTH PAIN RELIEF
NDC: 57896-206 | Form: SUSPENSION
Manufacturer: GERI-CARE PHARMACEUTICAL CORP
Category: otc | Type: HUMAN OTC DRUG LABEL
Date: 20251231

ACTIVE INGREDIENTS: ACETAMINOPHEN 500 mg/15 mL
INACTIVE INGREDIENTS: CITRIC ACID MONOHYDRATE; FD&C RED NO. 40; METHYLPARABEN; POLYETHYLENE GLYCOL, UNSPECIFIED; SUCRALOSE; PROPYLENE GLYCOL; PROPYLPARABEN; WATER; SODIUM CITRATE

GerCare- APAP SUS Extra 206

Active ingredient (in each 15mL Tablespoonful)

Acetaminophen 500 mg

Purpose

Pain reliever/Fever reducer

Uses

- temporarily relieves minor aches and pains
- temporarily reduces fever

Warnings

Liver Warning:This product contains acetaminophen. The maximum
daily dose of this product is 6 tablespoonfuls in 24 hours.
Severe liver damage may occur if you take
• more than 8 tablespoonfuls (4,000 mg of acetaminophen) in 24
hours • with other drugs containing acetaminophen
• 3 or more alcoholic drinks every day while using this product
Allergy alert:acetaminophen may cause severe skin reactions.
Symptoms may include: • skin reddening • blisters • rash
If a skin reaction occurs, stop use and seek medical help right away.

Do not use

- with any other drug containing acetaminophen (prescription or non-prescription). If you are not sure whether a drug contains acetaminophen, ask a doctor or pharmacist.
- if you are allergic to acetaminophen or any of the inactive ingredients in this product

Ask a doctor before use if you haveliver disease

Ask a doctor or pharmacist before use if you aretaking the blood thinning drug warfarin

When using this product: Do not exceed recommended dose.

Stop use and ask a doctor if

- new symptoms occur
- redness or swelling is present
- pain gets worse or lasts more than 10 days
- fever gets worse or lasts more than 3 days

These could be signs of a serious condition.

KEEP OUT OF REACH OF CHILDREN

If pregnant or breastfeeding,ask a health professional before use.

Keep out of reach of children.

Overdose warning

In case of overdose, get medical help or contact a Poison Control Center right away. Quick medical attention is critical for adults/children even if you do not notice any signs or symptoms.

Directions

- do not take more than directed

Adults and children 12 years of age and older | Take 1 to 2 Tablespoons every 4 to 6 hours as needed; not more than 6 Tablespoons in 24 hours. Do not take for more than 10 days unless directed by a doctor
Children under 12 years | ask a doctor

Other information

- store at room temperature 15°- 30°C (59°-86°F)
- protect from freezing
- protect from light
- TAMPER-EVIDENT: Do not use if foil seal over bottle opening is torn, broken or missing.

Inactive ingredients

artificial and natural cherry flavor, citric acid, FD&C Red #40, methylparaben, polyethylene glycol, propylene glycol, propylparaben, purified water, sodium citrate, sucralose

Questions or comments?

1-800-540-3765

RECENT MAJOR CHANGES

correct typographical errors in dosage section